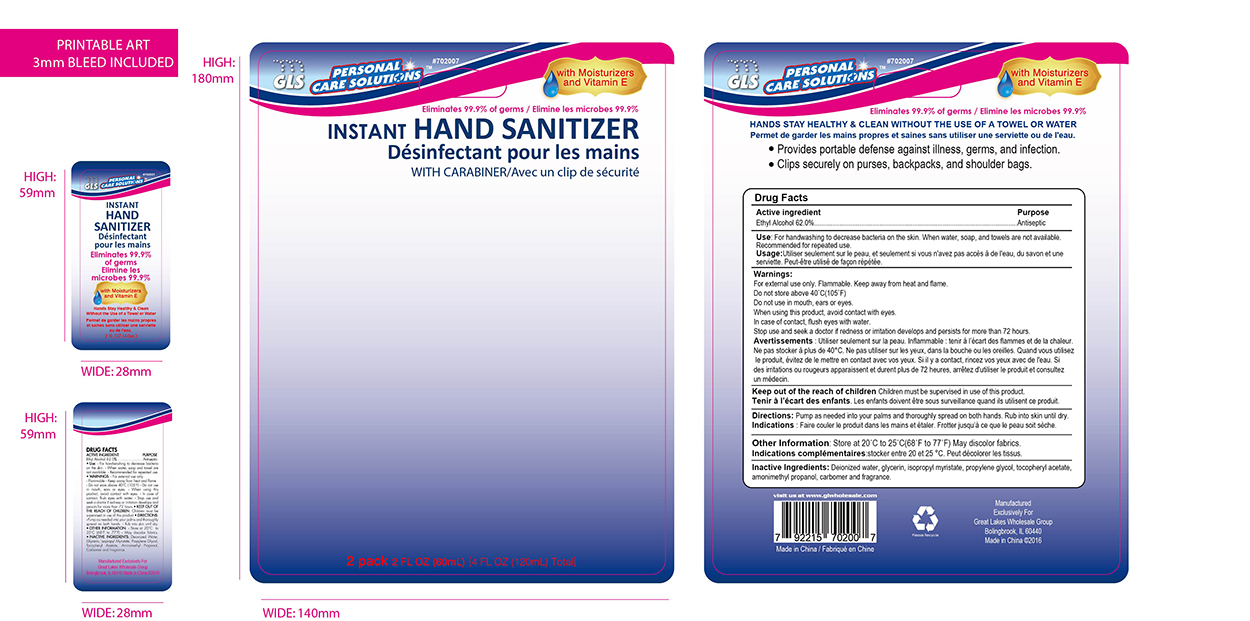 DRUG LABEL: skin protectant
NDC: 64092-307 | Form: LIQUID
Manufacturer: Great Lakes Wholesale, Marketing, and Sales, Inc
Category: otc | Type: HUMAN OTC DRUG LABEL
Date: 20160830

ACTIVE INGREDIENTS: ALCOHOL 74.4 mL/120 mL
INACTIVE INGREDIENTS: WATER

DESCRIPTION

GLS PERSONAL CARE SOLUTIONS

INSTANT HAND SANITIZER

with carabiner

With Moisturizers and Vitamin E

Elimates 99.9% of germs

2 pack 2 FL. OZ. (60mL) [4 FL OZ (120 mL) total]

Active Ingredient Purpose

Ethyl Alcohol..........................................................................Antiseptic

PURPOSE

Decrease bacteria on the skin.

INDICATIONS AND USAGE

For handwashing when water, soap and towels are not available.

Recommended for repeated use.

Clips securely on purses, backpacks and shoulder bags.

Provides portable defense against illness, germs and infection.

WARNINGS

For external use Only

Flammable. Keep away from heat and flame.

Do not store above 40°C(105°F)

Do not use in mouth, ears or eyes.

When using this product, avoid contact with eyes.

In case of contact, flush eyes with water.

Stop use and seek a doctor if redness or irritation develops and persists for more than 72 hours

KEEP OUT OF REACH OF CHILDREN

Chidren must be supervised in use of this product.

INSTRUCTIONS FOR USE

Pump as needed into your palms and thoroughly spread on both hands.

Rub into skin until dry.

DOSAGE AND ADMINISTRATION

Hand wash when water, soap and towel are not availabe.

62% Ethyl Alcohol.

STORAGE AND HANDLING

Store at 20°C to 25°C (68°F to 77°F)

May discolor fabrics.

INACTIVE INGREDIENT

Deionized water, glycerin, isopropyl myristate, propylene glycol, tocopheryl acetate, amonimethyl propanol, carbomer and fragrance.